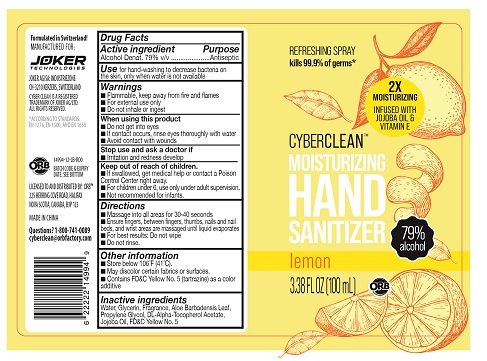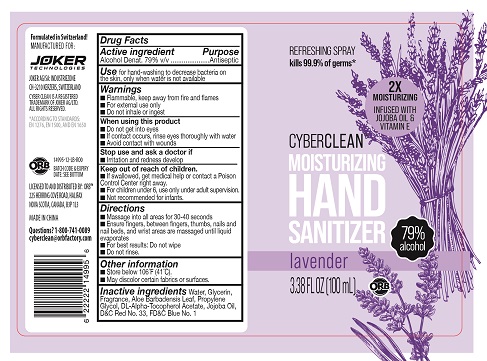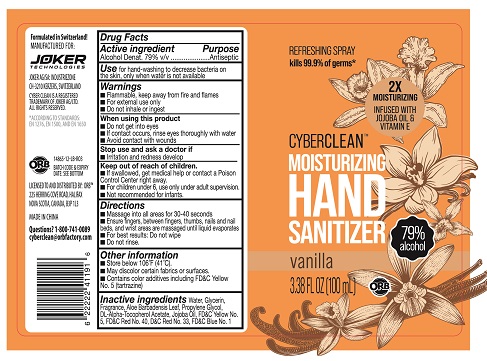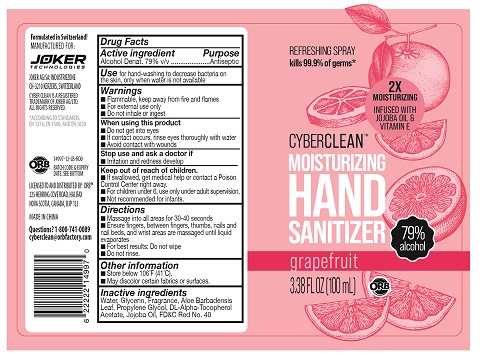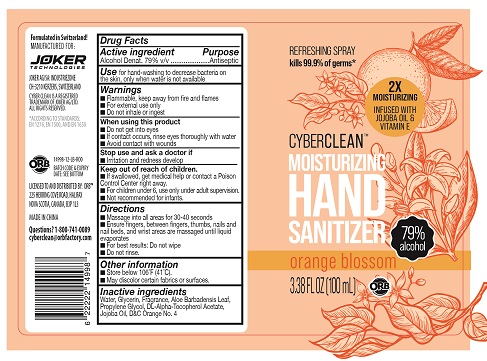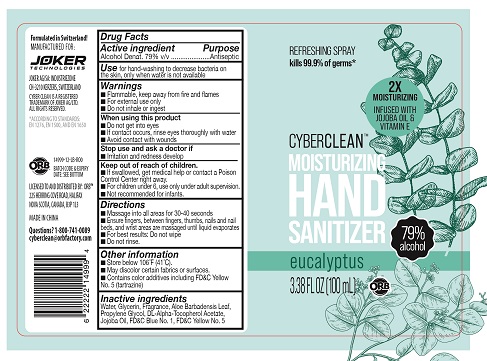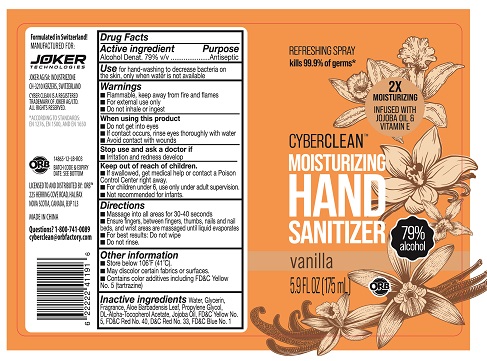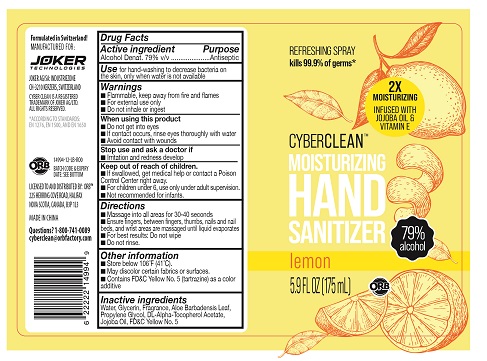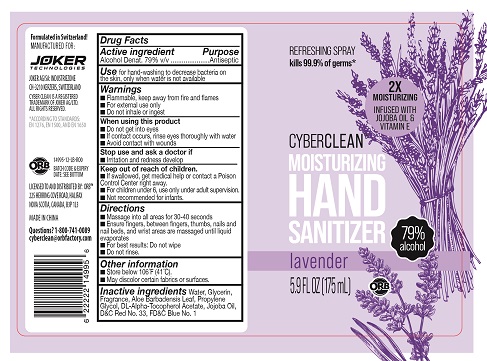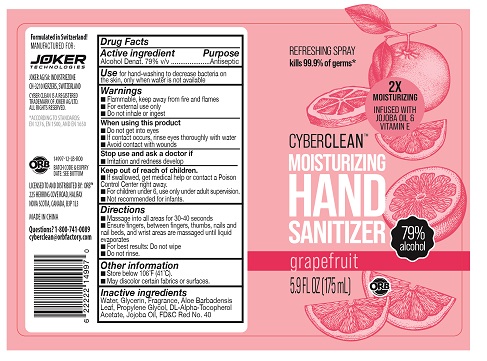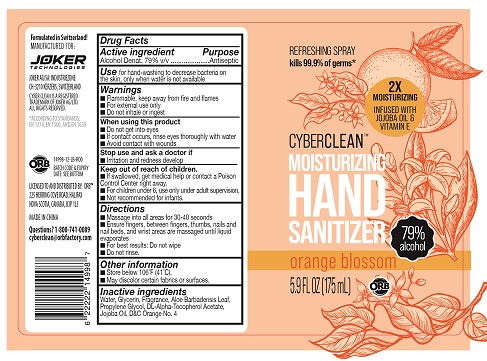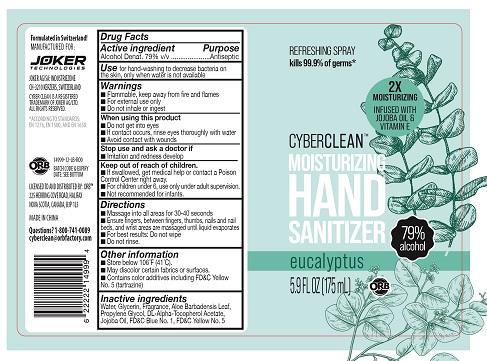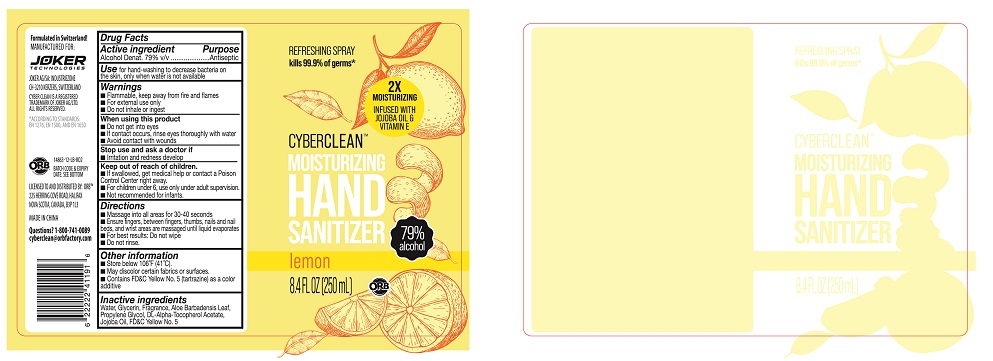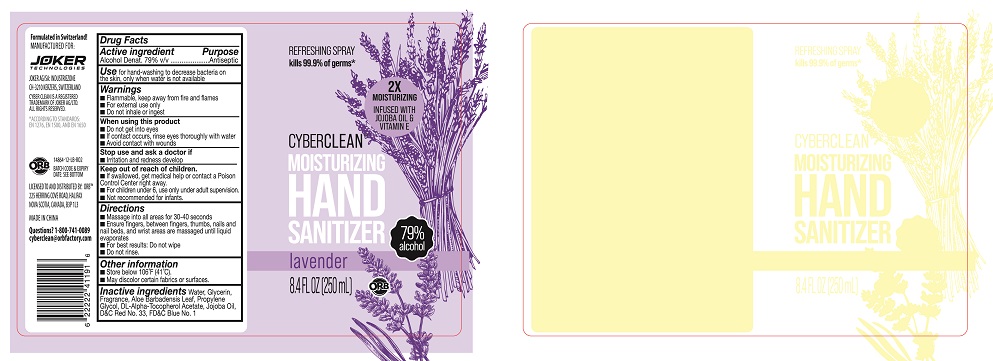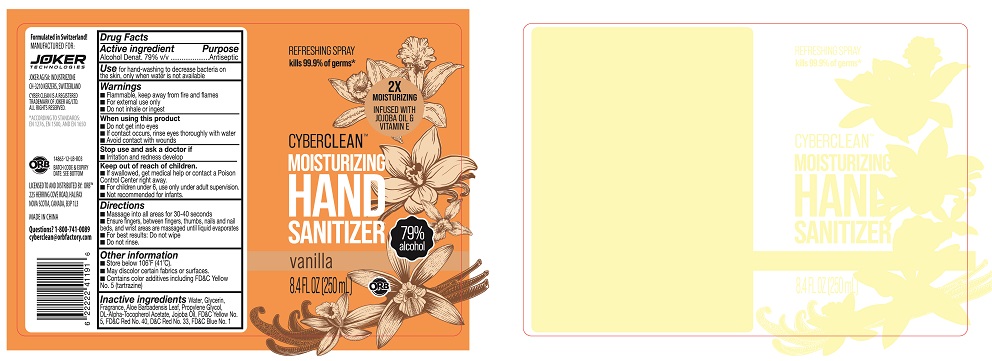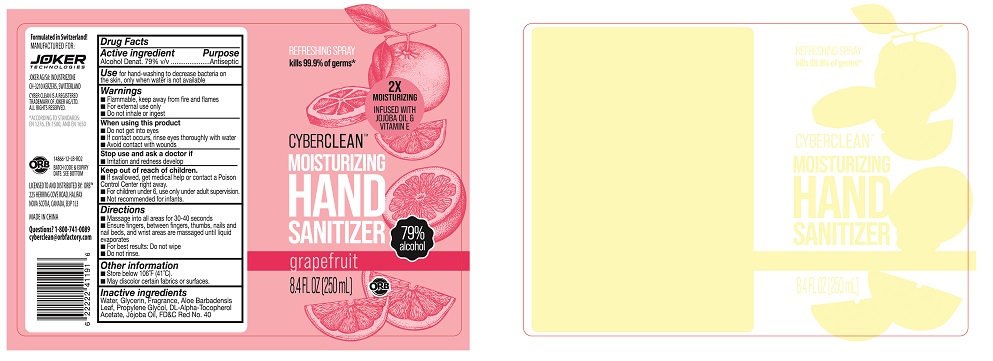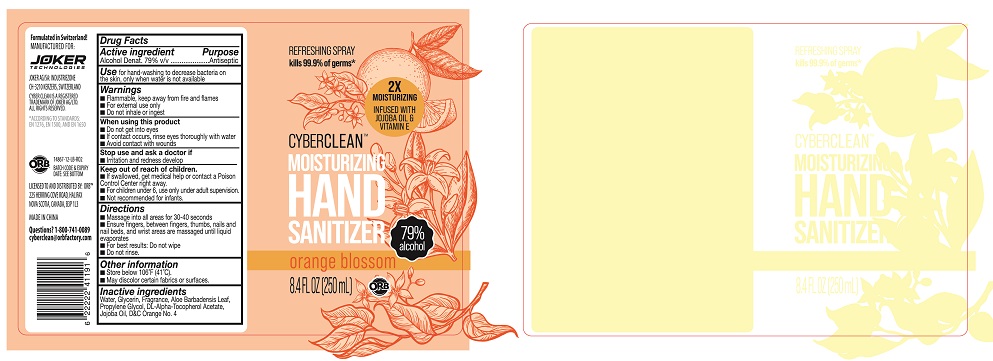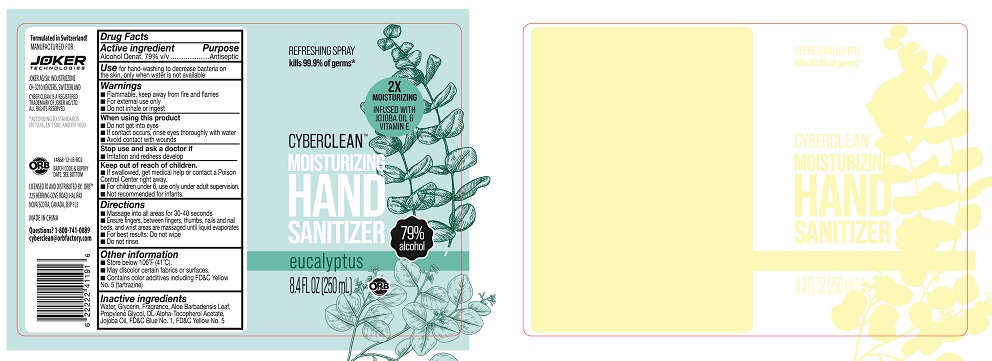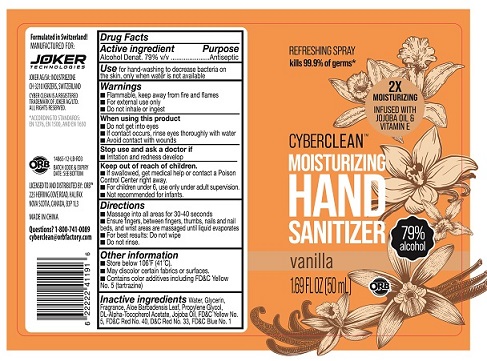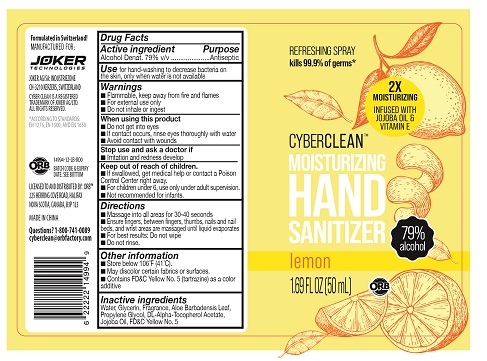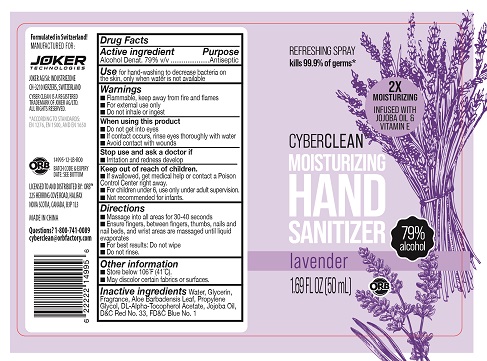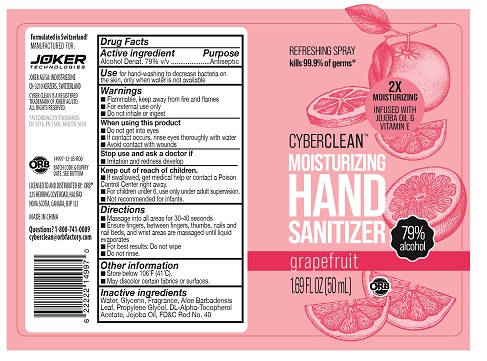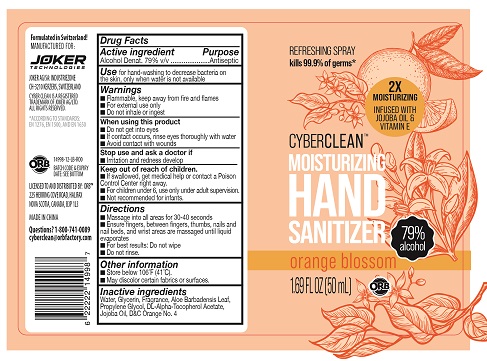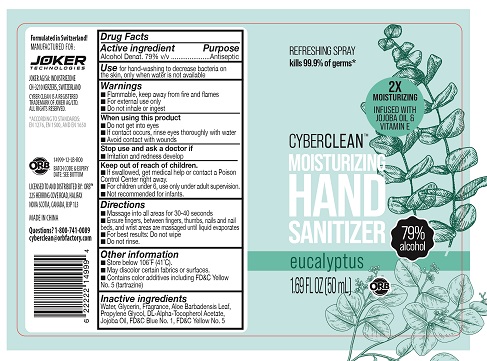 DRUG LABEL: Cyber Clean Moisturizing Hand SanitizerSpray Lemon
NDC: 75757-124 | Form: LIQUID
Manufacturer: JOKER AG
Category: otc | Type: HUMAN OTC DRUG LABEL
Date: 20210125

ACTIVE INGREDIENTS: ALCOHOL 79 mL/100 mL
INACTIVE INGREDIENTS: FD&C YELLOW NO. 5; JOJOBA OIL; ALPHA-TOCOPHEROL ACETATE; PROPYLENE GLYCOL; GLYCERIN; ALOE VERA LEAF; WATER

Cyber Clean Moisturizing Hand Sanitizer Spray Grapefruit
Cyber Clean Moisturizing Hand Sanitizer Spray Lemon
Cyber Clean Moisturizing Hand Sanitizer Spray Vanilla
Cyber Clean Moisturizing Hand Sanitizer Spray Orange Blossom
Cyber Clean Moisturizing Hand Sanitizer Spray Lavender
Cyber Clean Moisturizing Hand Sanitizer Spray Eucalyptus

Cyber Clean Moisturizing Hand Sanitizer Spray Grapefruit
Cyber Clean Moisturizing Hand Sanitizer Spray Lemon
Cyber Clean Moisturizing Hand Sanitizer Spray Vanilla
Cyber Clean Moisturizing Hand Sanitizer Spray Orange Blossom
Cyber Clean Moisturizing Hand Sanitizer Spray Lavender
Cyber Clean Moisturizing Hand Sanitizer Spray Eucalyptus

Active Ingredient(s)

Alcohol 79% v/v. Purpose: Antiseptic

Purpose

Antiseptic, Hand Sanitizer

Use

Hand Sanitizer to help reduce bacteria that potentially can cause disease. For use when soap and water are not available.

Warnings

For external use only. Flammable. Keep away from heat or flame

Do not use

- in children less than 2 months of age
- on open skin wounds

When using this product keep out of eyes, ears, and mouth. In case of contact with eyes, rinse eyes thoroughly with water.
Stop use and ask a doctor if irritation or rash occurs. These may be signs of a serious condition.
Keep out of reach of children. If swallowed, get medical help or contact a Poison Control Center right away.

Stop use and ask a doctor if irritation or rash occurs. These may be signs of a serious condition.

Keep out of reach of children. If swallowed, get medical help or contact a Poison Control Center right away.

Directions

- Massage into all areas for 30-40 seconds
- Ensure fingers, between fingers, thumbs, nails and nail beds, and wrist areas are massaged until liquid evaporates
- For best results: Do not wipe
- Do not rinse

Other information

- Store between 15-30C (59-86F)
- Avoid freezing and excessive heat above 40C (104F)

Inactive ingredients

Cyber Clean Moisturizing Hand SanitizerSpray Grapefruit:

Water
Glycerol
Aloe barbadensis leaf extract
Propylene Glycol
FD&C Red 40
Tocopheryl acetate
Jojoba Oil

Cyber Clean Moisturizing Hand SanitizerSpray Lemon:

Water
Glycerol
Aloe barbadensis leaf extract
Propylene Glycol
FD&C Yellow 5
Tocopheryl acetate
Jojoba Oil

Cyber Clean Moisturizing Hand SanitizerSpray Vanilla:

Water
Glycerol
Aloe barbadensis leaf extract
Propylene Glycol
D&C Red 33
FD&C Yellow 5
FD&C Red 40
FD&C Blue 1
Tocopheryl acetate
Jojoba Oil

Cyber Clean Moisturizing Hand SanitizerSpray Orange Blossom:

Water
Glycerol
Aloe barbadensis leaf extract
Propylene Glycol
D&C Orange 4
Tocopheryl acetate
Jojoba Oil

Cyber Clean Moisturizing Hand SanitizerSpray Lavender:

Water
Glycerol
Aloe barbadensis leaf extract
Propylene Glycol
D&C Red 33
FD&C Blue 1
Tocopheryl acetate
Jojoba Oil

Cyber Clean Moisturizing Hand SanitizerSpray Eucalyptus:

Water
Glycerol
Aloe barbadensis leaf extract
Propylene Glycol
FD&C Yellow 5
FD&C Blue 1
Tocopheryl acetate
Jojoba Oil